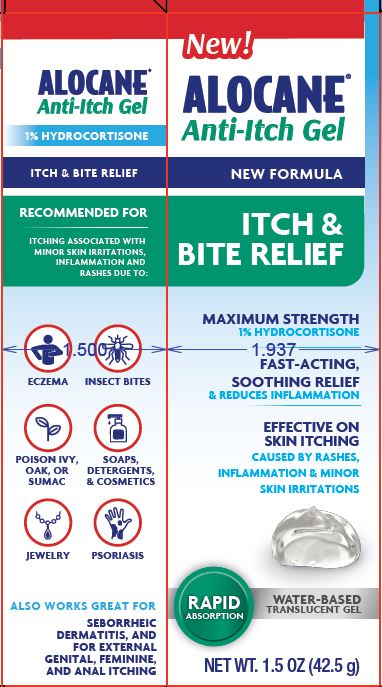 DRUG LABEL: Alocane Anti-Itch
NDC: 68229-411 | Form: GEL
Manufacturer: Quest Products, LLC
Category: otc | Type: HUMAN OTC DRUG LABEL
Date: 20260218

ACTIVE INGREDIENTS: HYDROCORTISONE 1 g/100 g
INACTIVE INGREDIENTS: HYPROMELLOSE, UNSPECIFIED; PHENOXYETHANOL; WATER; ETHYLHEXYLGLYCERIN; ALOE BARBADENSIS LEAF JUICE; ALCOHOL; PROPANEDIOL

Alocane Anti-Itch

Active Ingredient

Hydrocortisone 1%

Purpose

Anti-Itch

Uses

For the temporary relief of itching associated with minor skin irritations, inflamation, and rashes due to

- eczema
- insect bites
- poison ivy, poison oake, or poison sumac
- soaps
- detegents
- cosmetics
- jewelry
- seborrheic dermatitis
- psoriasis
- and for external genital, feminine, and anal itching

Warnings

FOR EXTERNAL USE ONLY

When using this product avoid contact with eyes

Stop use and ask a doctor

- if condition worsens, or if symptoms persist for more than 7 days or clear up and occur again within a few days
- stop use of this product and do not begin use of any other hydrocortisone product unless you have consulted a doctor.

Do not use

- for the treatment of diaper rash
- Do not use if you have vaginal discharge. Consult a doctor.
- Do not exceed the recommended daily dosage unless directed by a doctor.
- In case of bleeding, consult a doctor promptly.
- Do not put this product into the rectum by using fingers or any mechanical device or applicator.

Kep out of reach of children

If swallowed, get medical help or contact Poison Control Center reight away.

Directions

Adults and Children 2 years of age or older

- Apply to affected area not more than 3 to 4 times daily.
- Adults: when practical, cleans the affected area with mild soap and warm water and rinse thoroughly.
- Gently dry by patting or blotting with toilet tissue or soft cloth before application of this product.

Children under 2 years of age: Do not use, consult a doctor.

For external anal itching:

- Adults: when practical cleanse the affected area with mild soap and warm water and rinse thoroughly.
- Gently dry by patting or blotting with toilet tissue or soft cloth before application of this product.

Children Under 12 years of age: consult a doctor.

Other Information

Store at room temperature 15° - 30° C (59° - 86°F)

Inactive Ingredients

Aloe Barbadensis Leaf Juice, Ethylhexylglycerin, Hypromellose, Phenoxyethanol, Propanediol, SD Alcohol 40-B, Water.